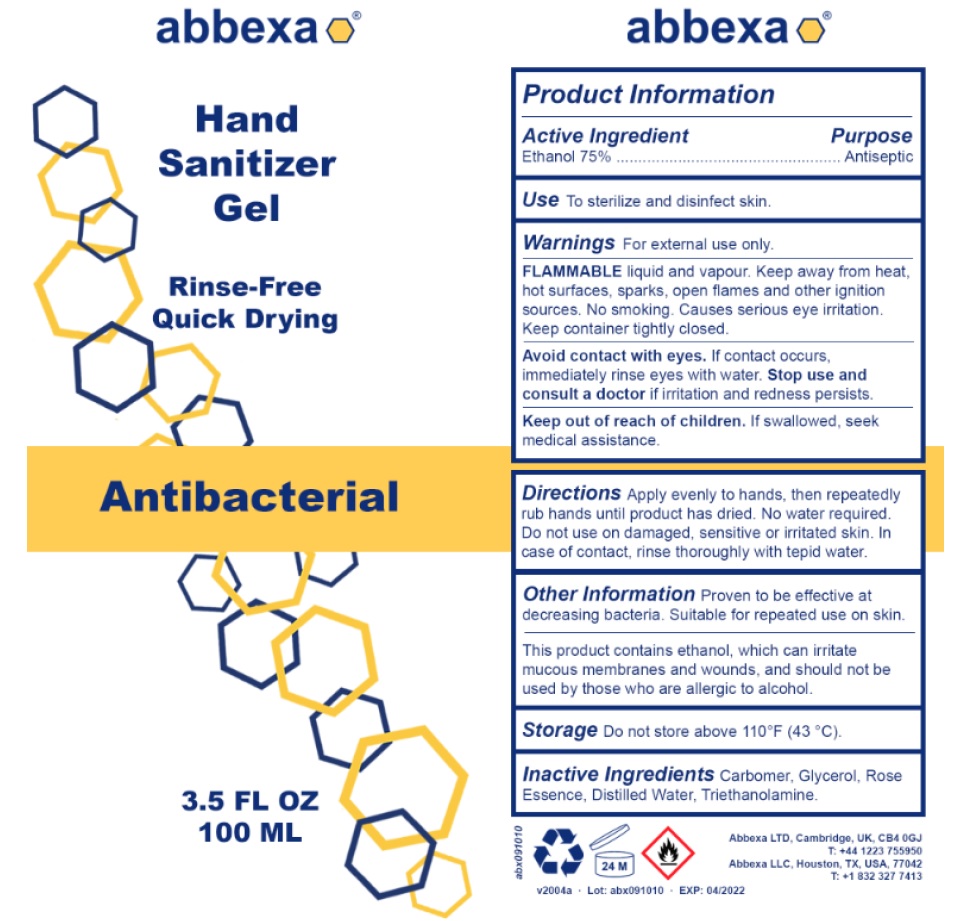 DRUG LABEL: Abbexa Hand Sanitizer
NDC: 74029-100 | Form: GEL
Manufacturer: ABBEXA LTD
Category: otc | Type: HUMAN OTC DRUG LABEL
Date: 20200402

ACTIVE INGREDIENTS: ALCOHOL 75 mL/100 mL
INACTIVE INGREDIENTS: CARBOMER HOMOPOLYMER, UNSPECIFIED TYPE; GLYCERIN; WATER; TROLAMINE

Abbexa Hand Sanitizer Gel

Active Ingredient

Ethanol 75%

Purpose

Antiseptic

INDICATIONS AND USAGE

Use To sterilize and disinfect skin.

Warnings For external use only.

FLAMMABLE liquid and vapour. Keep away from heat, hot surfaces, sparks, open flames and other ignition sources. No smoking. Causes serious eye irritation. Keep container tightly closed.

Avoid contact with eyes. If contact occurs, immediately rinse eyes with water. Stop use and consult a doctor if irritation and redness persists.

Keep out of reach of children. If swallowed, seek medical assistance.

DOSAGE AND ADMINISTRATION

Directions Apply evenly to hands, then repeatedly rub hands until product has dried. No water required. Do not use on damaged, sensitive or irritated skin. In case of contact, rinse thoroughly with tepid water.

Other Information Proven to be effective at decreasing bacteria. Suitable for repeated use on skin.

This product contains ethanol, which can irritate mucous membranes and wounds, and should not be used by those who are allergic to alcohol.

STORAGE AND HANDLING

Storage Do not store above 110°F (43 °C).

INACTIVE INGREDIENT

Inactive Ingredients Carbomer, Glycerol, Rose Essence, Distilled Water, Triethanolamine.

Rinse-Free

Quick Drying

Antibacterial

Abbexa LTD, Cambridge, UK, CB4 0GJ

T: +44 1223 755950
Abbexa LLC, Houston, TX, USA, 77042
T: +1 832 327 7413